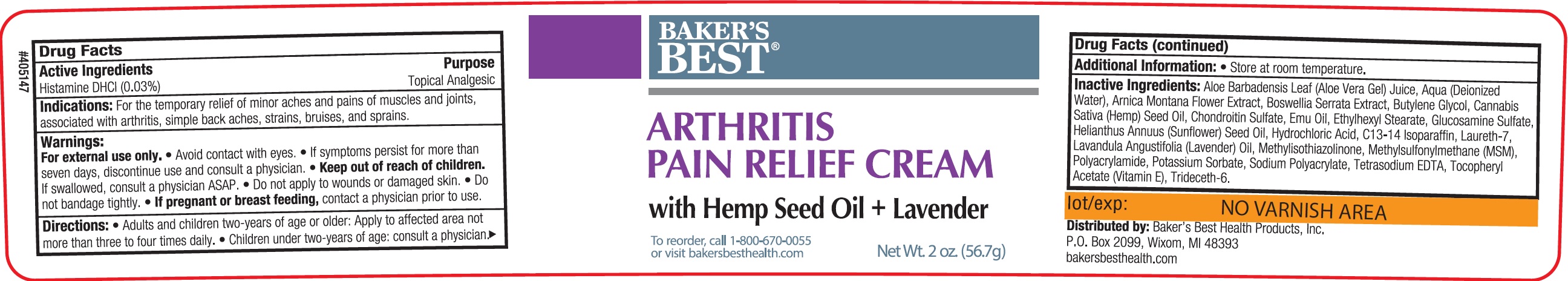 DRUG LABEL: BAKERS BEST Arthritis Pain Relief Cream with Hemp and Lavender
NDC: 76102-329 | Form: CREAM
Manufacturer: BAKER'S BEST HEALTH PRODUCTS, INC.
Category: otc | Type: HUMAN OTC DRUG LABEL
Date: 20231106

ACTIVE INGREDIENTS: HISTAMINE DIHYDROCHLORIDE 0.3 mg/1 g
INACTIVE INGREDIENTS: ALOE VERA LEAF; WATER; ARNICA MONTANA FLOWER; INDIAN FRANKINCENSE; BUTYLENE GLYCOL; CANNABIS SATIVA SEED OIL; EMU OIL; ETHYLHEXYL STEARATE; GLUCOSAMINE SULFATE; SUNFLOWER OIL; HYDROCHLORIC ACID; C13-14 ISOPARAFFIN; LAURETH-7; LAVENDER OIL; METHYLISOTHIAZOLINONE; DIMETHYL SULFONE; POTASSIUM SORBATE; EDETATE SODIUM; .ALPHA.-TOCOPHEROL ACETATE; TRIDECETH-6

BAKER'S BEST Arthritis Pain Relief Cream with Hemp and Lavender

Active Ingredients

Histamine DHCL (0.03%)

Purpose

Topical Analgesic

Indications:

For the temporary relief of minor aches and pains of muscles and joints, associated with arthritis, simple back aches, strains, bruises, and sprains.

Warnings:

For external use only.

- Avoid contact with eyes.
- If symptoms persist for more than seven days, discontinue use and consult a physician.

Keep out of reach of children.

- If swallowed, consult a physician ASAP.
- Do not apply to wounds or damaged skin.
- Do not bandage tightly.

If pregnant or breast feeding,

- contact a physician prior to use.

Directions:

- Adults and children two-years of age or older: Apply to affected area not more than three to four times daily.
- Children under two-years of age: consult a physician.

Additional Information:

- Store at room temperature.

Inactive Ingredients:

Aloe Barbadensis Leaf (Aloe Vera Gel) Juice, Aqua (Deionized Water), Arnica Montana Flower Extract, Boswellia Serrata Extract, Butylene Glycol, Cannabis Sativa (Hemp) Seed Oil, Chondroitin Sulfate, Emu Oil, Ethylhexyl Stearate, Glucosamine Sulfate, Helianthus Annuus (Sunflower) Seed Oil, Hydrochloric Acid, C13-14 Isoparaffin, Laureth-7, Lavandula Angustifolia (Lavender) Oil, Methylisothiazolinone, Methylsulfonylmethane (MSM), Polyacrylamide, Potassium Sorbate, Sodium Polyacrylate, Tetrasodium EDTA, Tocopheryl Acetate (Vitamine E), Trideceth-6.